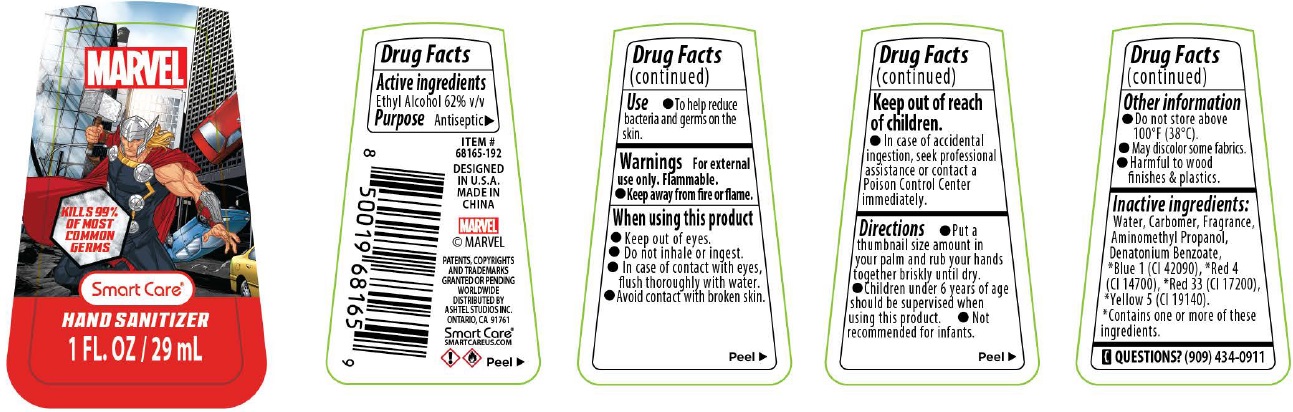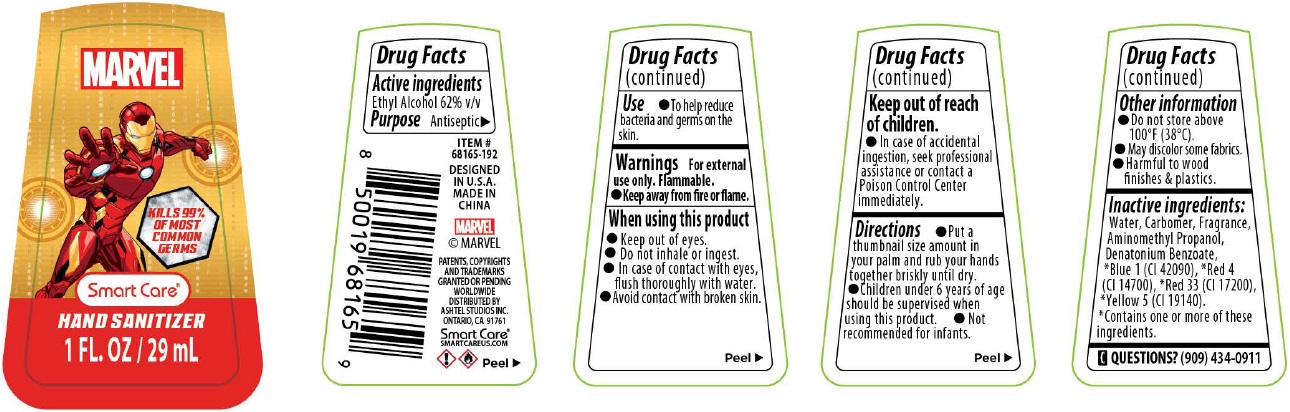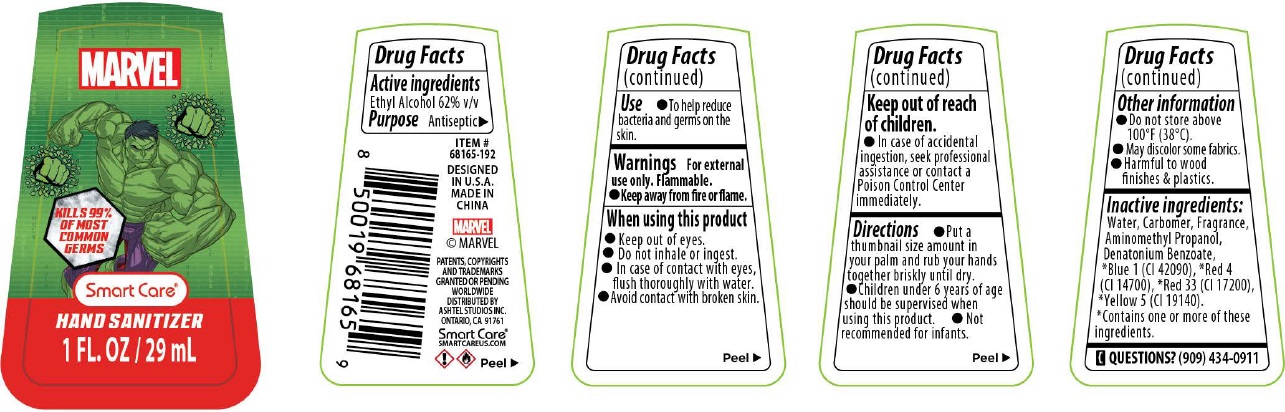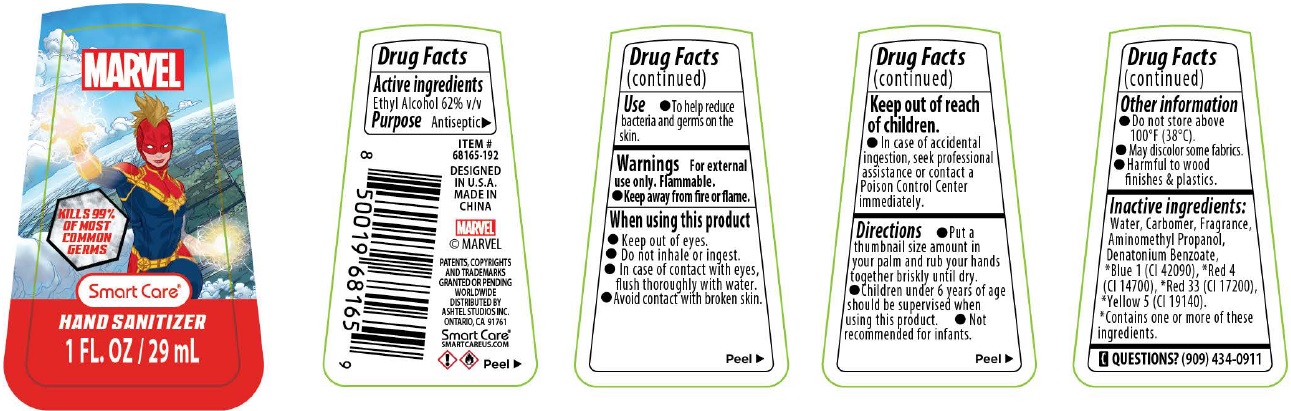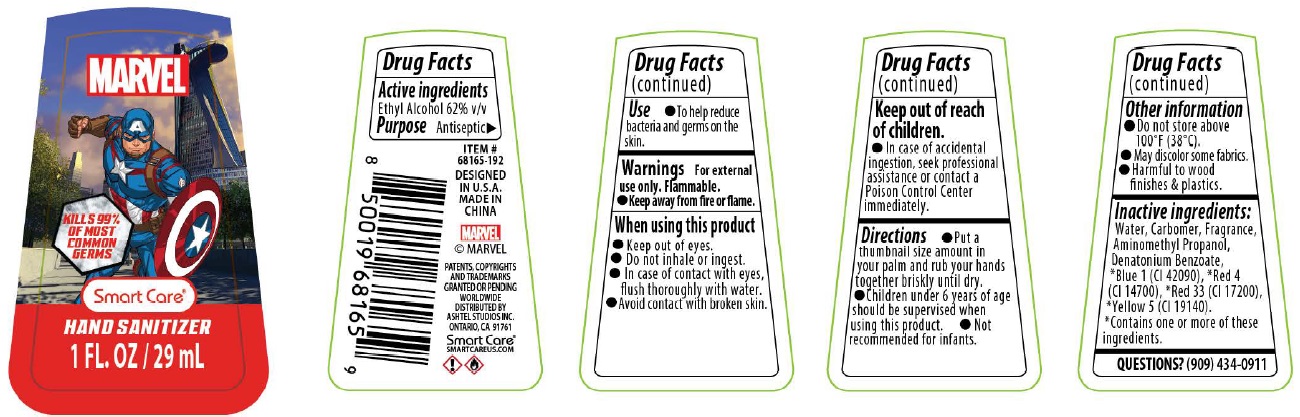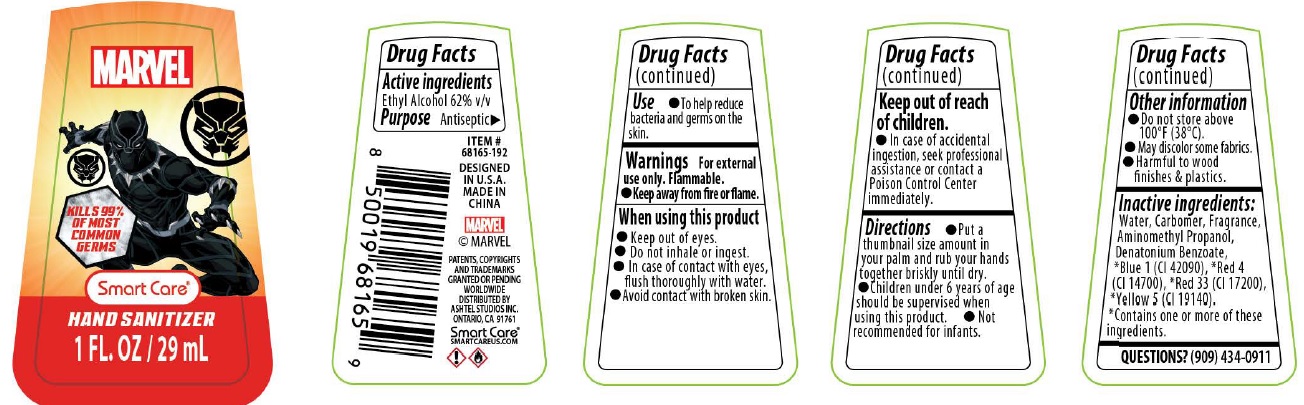 DRUG LABEL: Smart Care Marvel Hand Sanitizer
NDC: 54860-350 | Form: GEL
Manufacturer: Shenzhen Lantern Science Co., ltd.
Category: otc | Type: HUMAN OTC DRUG LABEL
Date: 20230512

ACTIVE INGREDIENTS: ALCOHOL 62 mL/100 mL
INACTIVE INGREDIENTS: WATER; CARBOMER HOMOPOLYMER, UNSPECIFIED TYPE; AMINOMETHYLPROPANOL; DENATONIUM BENZOATE; FD&C BLUE NO. 1; FD&C RED NO. 4; D&C RED NO. 33; FD&C YELLOW NO. 5

MARVEL Smart Care* HAND SANITIZER

Active ingredients

Ethyl Alcohol 62% v/v

Purpose

Antiseptic

Use

• To help reduce bacteria and germs on the skin.

Warnings

For external use only. Flammable.

• Keep away from fire or flame.

When using this product

• Keep out of eyes.

• Do not inhale or ingest.

• In case of contact with eyes, flush thoroughly with water.

• Avoid contact with broken skin.

Keep out of reach of children.

• In case of accidental ingestion, seek professional assistance or contact a Poison Control Center immediately.

Directions

• Put a thumbnail size amount in your palm and rub your hands together briskly until dry.

• Children under 6 years of age should be supervised when using this product.

• Not recommended for infants.

Other information

• Do not store above 100˚F (38˚C).

• May discolor some fabrics.

• Harmful to wood finishes & plastics.

Inactive ingredients:

Water, Carbomer, Fragrance, Aminomethyl Propanol, Denatonium Benzoate, *Blue 1(CI 42090), *Red 4(CI 14700), *Red 33(CI 17200), *Yellow

5(CI 19140). *Contains one or more of these ingredients.

Questions?

(909)434-0911

KILLS 99% OF MOST COMMON GERMS

DESIGNED IN U.S.A.

MADE IN CHINA

© MARVEL

PATENTS, COPYRIGHTS AND TRADEMARKS GRANTED OR PENDING WORLDWIDE

DISTRIBUTED BY

ASHTEL STUDIOS INC.

ONTARIO, CA 91761

Smart Care*

SMARTCAREUS.COM